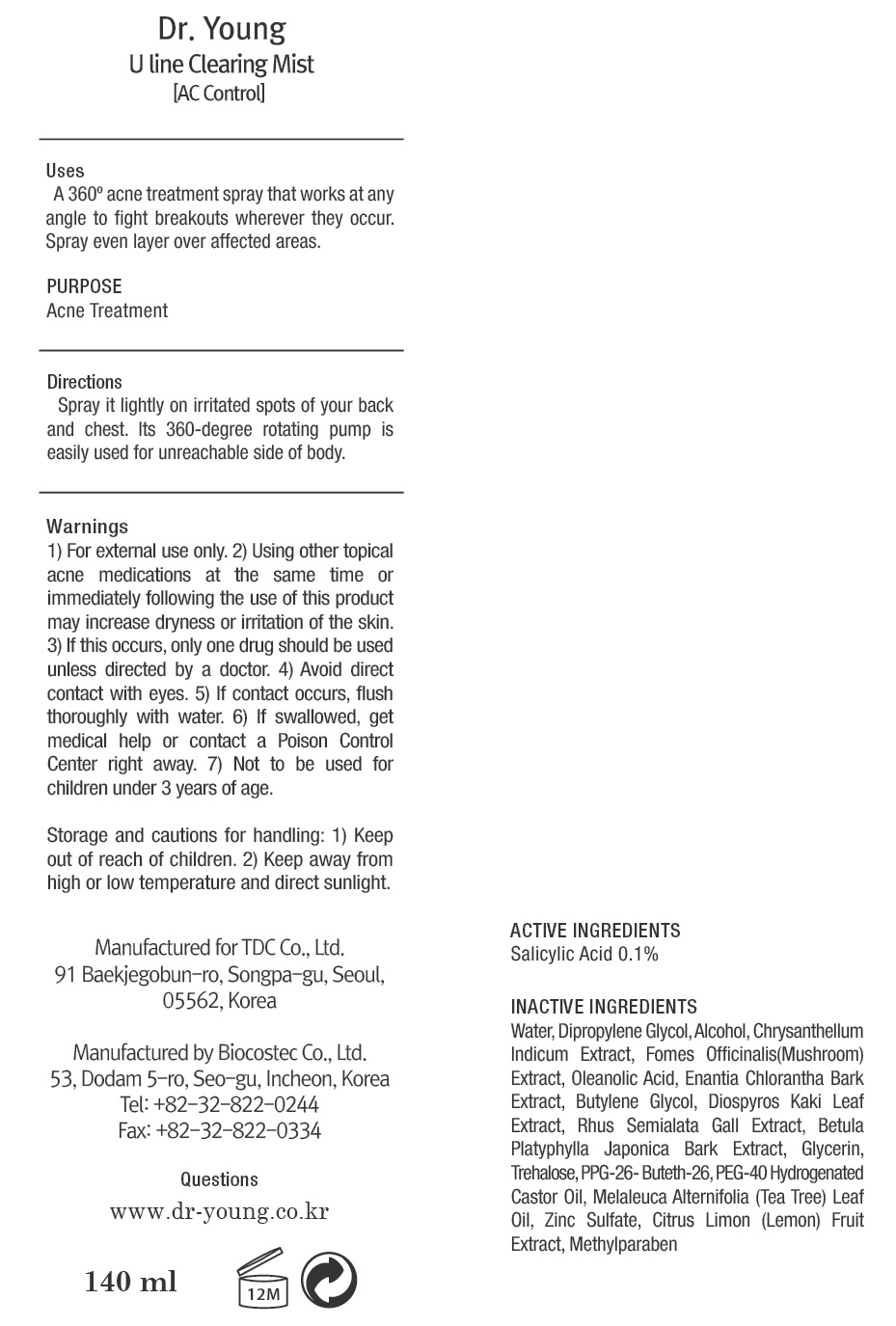 DRUG LABEL: Dr Young AC CONTROL U line Clearing Mist
NDC: 43948-1350 | Form: SPRAY
Manufacturer: Tdc, Co. Ltd
Category: otc | Type: HUMAN OTC DRUG LABEL
Date: 20181205

ACTIVE INGREDIENTS: Salicylic Acid 0.14 g/140 mL
INACTIVE INGREDIENTS: Water; Dipropylene Glycol

ACTIVE INGREDIENT

Active ingredients: Salicylic Acid 0.1%

INACTIVE INGREDIENT

Inactive ingredients: Water, Dipropylene Glycol, Alcohol, Chrysanthellum Indicum Extract, Fomes Officinalis(Mushroom) Extract, Oleanolic Acid, Enantia Chlorantha Bark Extract, Butylene Glycol, Diospyros Kaki Leaf Extract, Rhus Semialata Gall Extract, Betula Platyphylla Japonica Bark Extract, Glycerin, Trehalose, PPG-26- Buteth-26, PEG-40 Hydrogenated Castor Oil, Melaleuca Alternifolia (Tea Tree) Leaf Oil, Zinc Sulfate, Citrus Limon (Lemon) Fruit Extract, Methylparaben

PURPOSE

Purpose: Acne Treatment

WARNINGS

Warning: 1) For external use only. 2) Using other topical acne medications at the same time or immediately following the use of this product may increase dryness or irritation of the skin. 3) If this occurs, only one drug should be used unless directed by a doctor. 4) Avoid direct contact with eyes. 5) If contact occurs, flush thoroughly with water. 6) If swallowed, get medical help or contact a Poison Control Center right away. 7) Not to be used for children under 3 years of age.

Storage and cautions for handling: 1) Keep out of reach of children. 2) Keep away from high or low temperature and direct sunlight.

KEEP OUT OF REACH OF CHILDREN

Uses

Uses: A 360 acne treatment spray that works at any angle to fight breakouts wherever they occur. Spray even layer over affected areas.

Directions

Directions: Spray it lightly on irritated spots of your back and chest. Its 360-degree rotating pump is easily used for unreachable side of body.